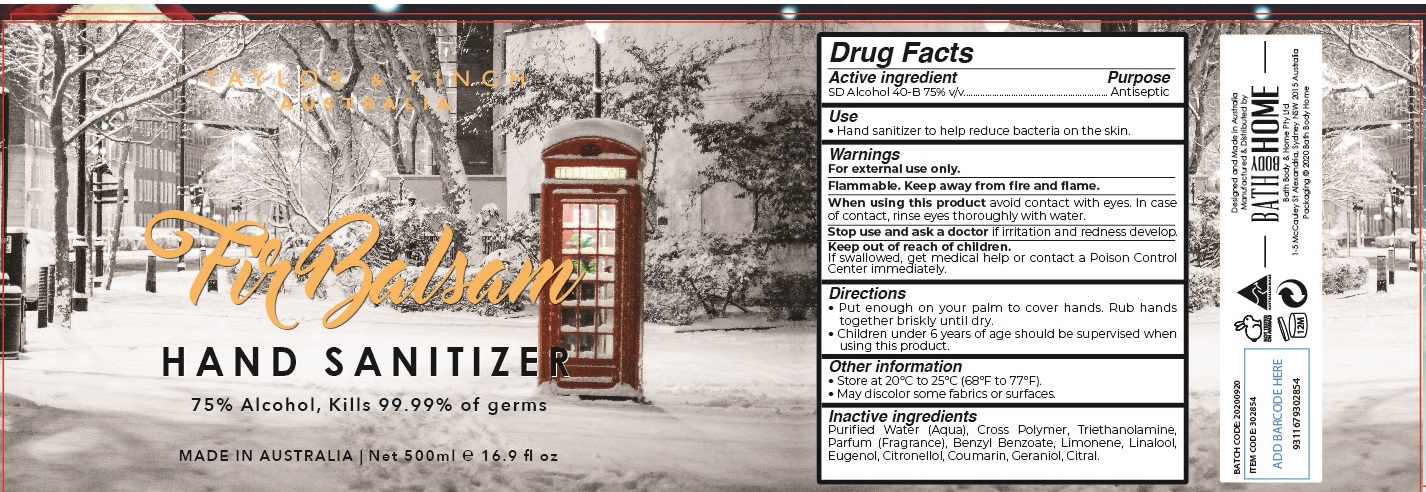 DRUG LABEL: Taylor and Finch XMAS Fir Balsam Hand Sanitizer
NDC: 79978-012 | Form: GEL
Manufacturer: COGNESCENTI PTY. LTD.
Category: otc | Type: HUMAN OTC DRUG LABEL
Date: 20200828

ACTIVE INGREDIENTS: ALCOHOL 75 mL/100 mL
INACTIVE INGREDIENTS: water; TROLAMINE; BENZYL BENZOATE; CITRAL

hand sanitizer

Active ingredient

SD Alcohol 40-B 75% v/v

Purpose

Antiseptic

USE

- hand sanitizer to help reduce bacteria on the skin.

Warnings

For external use only.

Flammable. Keep away from fire and flame.

When using this product

avoid contact with eyes. In case of contact, rinse eyes thoroughly with water.

Stop use and ask a doctor if

- irritation and redness develops.

Keep out of reach of children.

If swallowed, get medical help or contact a Poison Control Center right away.

Directions

- Put enough on you palm to cover hands. Rub hands together briskly until dry.
- Children under 6 years of age should be supervised when using this product.

Other information:

- Store at 20℃ to 25℃ (68℉ to 77℉).
- May discolor some fabrics or surface.

Inactive ingredients

Purified Water (Aqua), Cross Polymer, Triethanolamine, Parfum (Fragrance), Benzyl Benzoate, Limonene, Linalool, Citral, Eugenol, Citronellol, Coumarin, Geraniol